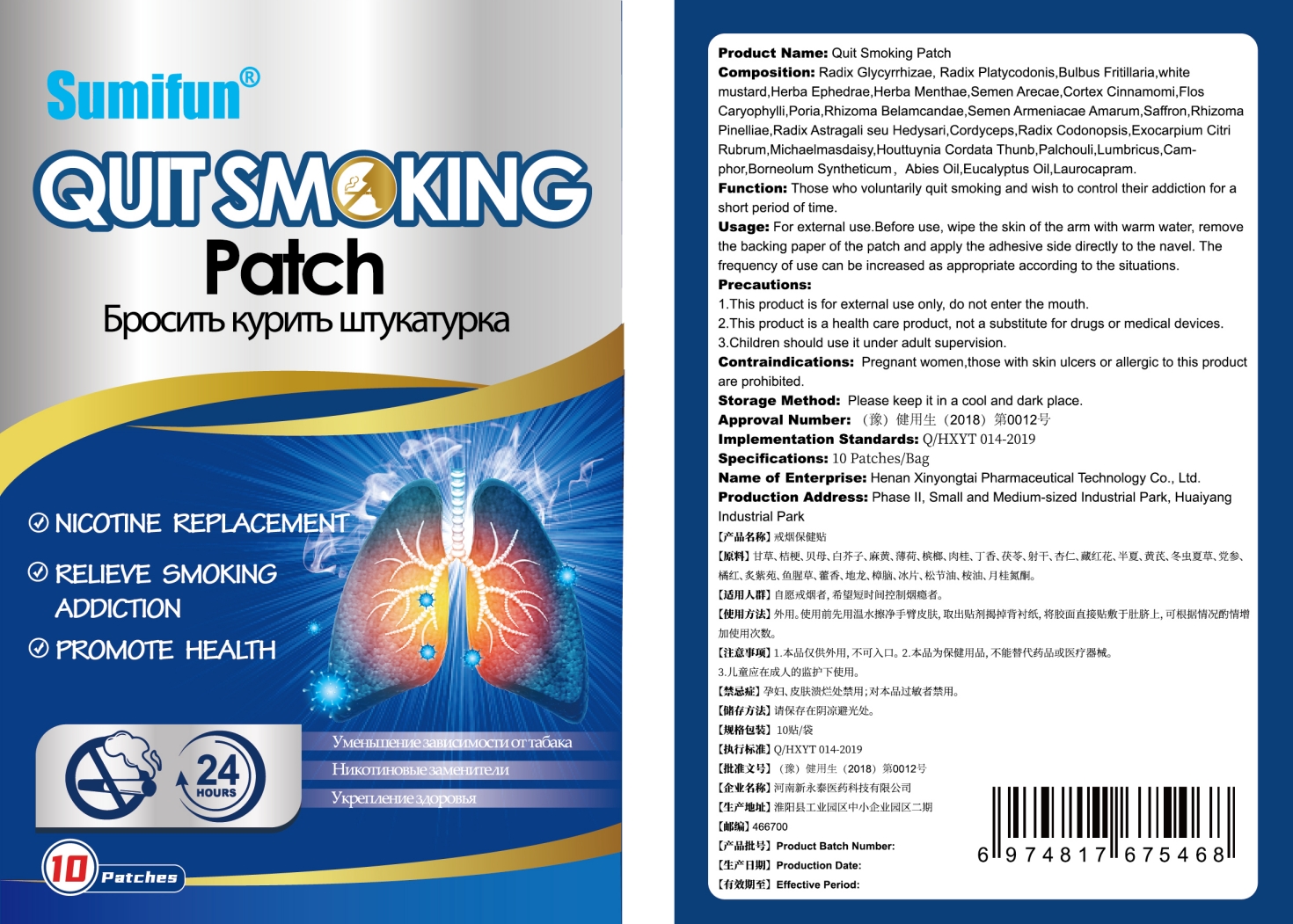 DRUG LABEL: Quit Smoking Patch
NDC: 83675-007 | Form: PATCH
Manufacturer: Guangzhou Hanhai Trading Co., Ltd
Category: otc | Type: HUMAN OTC DRUG LABEL
Date: 20230920

ACTIVE INGREDIENTS: LICORICE 14 g/100 1
INACTIVE INGREDIENTS: WHITE MUSTARD SEED; ARECA CATECHU SEED; FU LING; IRIS DOMESTICA ROOT; HOUTTUYNIA CORDATA WHOLE; CINNAMON; MENTHA ARVENSIS TOP; PHYLLOLOBIUM CHINENSE SEED; CLOTHIANIDIN; LAUROCAPRAM; EPHEDRA SINICA STEM; OPHIOCORDYCEPS SINENSIS; ANISE OIL; CLOVE; PRUNUS ARMENIACA SEED; PINELLIA TERNATA ROOT; BORNEOL; FRITILLARIA CIRRHOSA BULB; SAFFRON; LUMBROKINASE; CITRUS X AURANTIUM SEED; PLATYCODON GRANDIFLORUM ROOT; EUCALYPTUS OIL

83675-007

Active Ingredient

Radix Glvcvrrhizae 14.0%

Purpose

Relieve smoking addiction

Use

Quit Smoking Patch to help relieve smoking addiction

Warnings

For external use only. Do not take it internally.

Keep Out Of Reach Of Children
Prohibited for those with damaged skin.

Do not use

Product shall not be eat

When Using

Do not stick around eyes and mouth,This product cannot replace drugs.

Stop Use

In case of adverse reactions, please stop using this product.If the symptoms.

Ask Doctor

ask doctor in case of adverse reactions

Keep Oot Of Reach Of Children

Keep Out Of Reach Of Children

Directions

Take one piece of this product when needed, remove the waxpaper,

stick to the desired area and press the surrounding, replace it every 8-12 hours.

Children should be used under adult supervision.

Other information

Store the product in a cool, dry and well-ventilated place

Avoid direct sunlight

Inactive ingredients

Radix Platvcodonis

Bulbus Fritillaria.

white mustard

Herba Ephedrae.

Herba Menthae.

Semen Arecae.

Cortex Cinnamomi.

Flos Caryophylli

Poria,

Rhizoma Belamcandae,

Semen Armeniacae Amarum,

Saffron,

Rhizoma Pinelliae,

Radix Astragali seu Hedysari,

Cordyceps

Exocarpium Citri Rubrum,

Michaelmasdaisv,

Houttuvnia Cordata Thunb,

Palchouli,

LumbricusCam-phor,

Borneolum Svntheticum，

Abies Oil.

Eucalyptus Oil,

Laurocapram